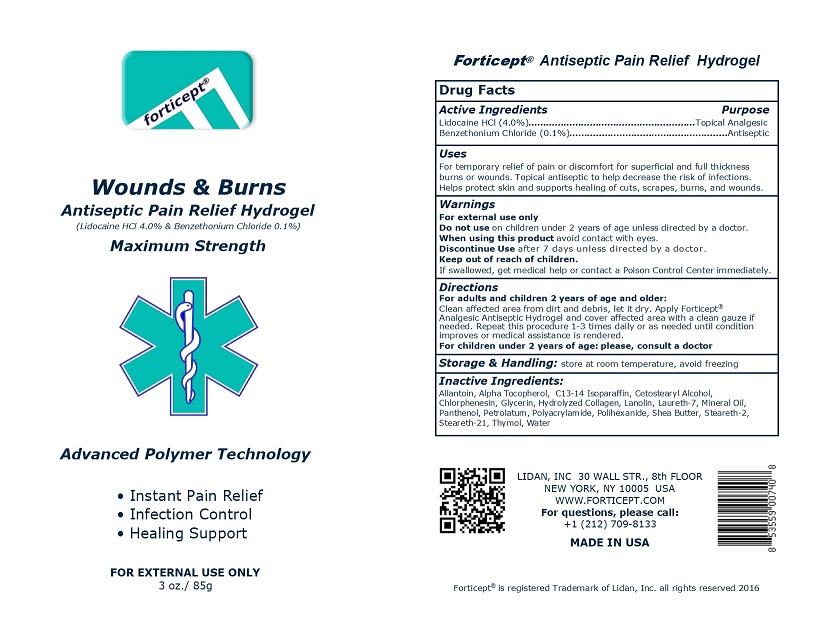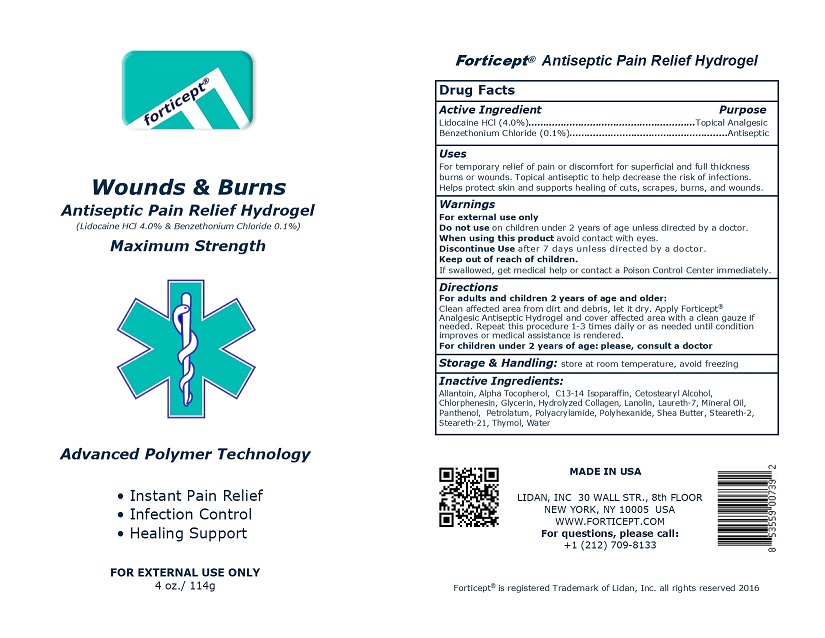 DRUG LABEL: Forticept Wounds and Burns Hydrogel
NDC: 72127-0803 | Form: GEL
Manufacturer: Lidan, inc.
Category: otc | Type: HUMAN OTC DRUG LABEL
Date: 20250325

ACTIVE INGREDIENTS: BENZETHONIUM CHLORIDE 0.001 kg/1 kg; LIDOCAINE 0.04 kg/1 kg
INACTIVE INGREDIENTS: ALLANTOIN; .ALPHA.-TOCOPHEROL ACETATE, DL-; C13-14 ISOPARAFFIN; CETOSTEARYL ALCOHOL; CHLORPHENESIN; DEXPANTHENOL; FD&C BLUE NO. 1; GLYCERIN; HYDROLYSED BOVINE COLLAGEN (ENZYMATIC; 2000-5000 MW); LANOLIN; LAURETH-7; MINERAL OIL; PETROLATUM; POLYACRYLAMIDE (10000 MW); POLIHEXANIDE; SHEA BUTTER; STEARETH-2; STEARETH-21; THYMOL; WATER

Forticept Wounds and Burns Hydrogel

DRUG FACTS

Active Ingredient/Purpose:

LIDOCAINE HCL (4.0%)..........................Topical Analgesic
BENZETHONIUM CHLORIDE (0.1%)....................Antiseptic

Uses:

For temporary relief of pain or discomfort for superficial and full thickness burns or wounds. Topical antiseptic to help decrease the risk of infections. Helps protect skin and supports healing of cuts, scrapes, burns, and wounds.

INDICATIONS AND USAGE

Topical analgesic - for temporary relief of pain or discomfort for superficial and full thickness burns or wounds.

Topical antiseptic - to help decrease the risk of wounf and skin infections.

WARNINGS:

For external use only!

Keep out of reach of children. If swallowed, get medical help or contact a Poison Control Center immidiately.

When using this product avoid contact with eyes.

Do not use on children under 2 years of age unless directed by a doctor.

STOP USE

Discontinue Use after 7 days unless directed by a doctor

Directions:

Adults and children 2 years of age and older:
• Clean affected area from dirt and debris, let it dry.
• Apply Forticept Analgesic Antiseptic Hydrogel and cover affected area with a clean gauze if needed.
• Repeat this procedure 1-3 times daily or as needed until condition improves or medical assistance is rendered.

ASK DOCTOR

For children under 2 years of age: please, consult a doctor

Inactive Ingredients:

ALLANTOIN, ALPHA TOCOPHEROL, C13-14 ISOPARAFFIN, CETOSTEARYL ALCOHOL, CHLORPHENESIN, D-PANTHENOL, FD&C BLUE #1, GLYCERIN, HYDROLYZED COLLAGEN, LANOLIN, LAURETH-7, PARAFFINUM LIQUIDUM, PETROLATUM, POLYACRYLAMIDE, POLYHEXANIDE, SHEA BUTTER, STEARETH-2, STEARETH-21, THYMOL, WATER

Storage and handling:

- Keep container closed when not in use.
- Store at room temperature, avoid freezing.
- Do not store below 32F/0^0C or above 95F/35^0C for extended periods of time.

For Questions:

Lidan, Inc.
30 Wall Street, 8th Floor
New York, NY 10005
www.forticept.com

Please call: +1 212 709-8133